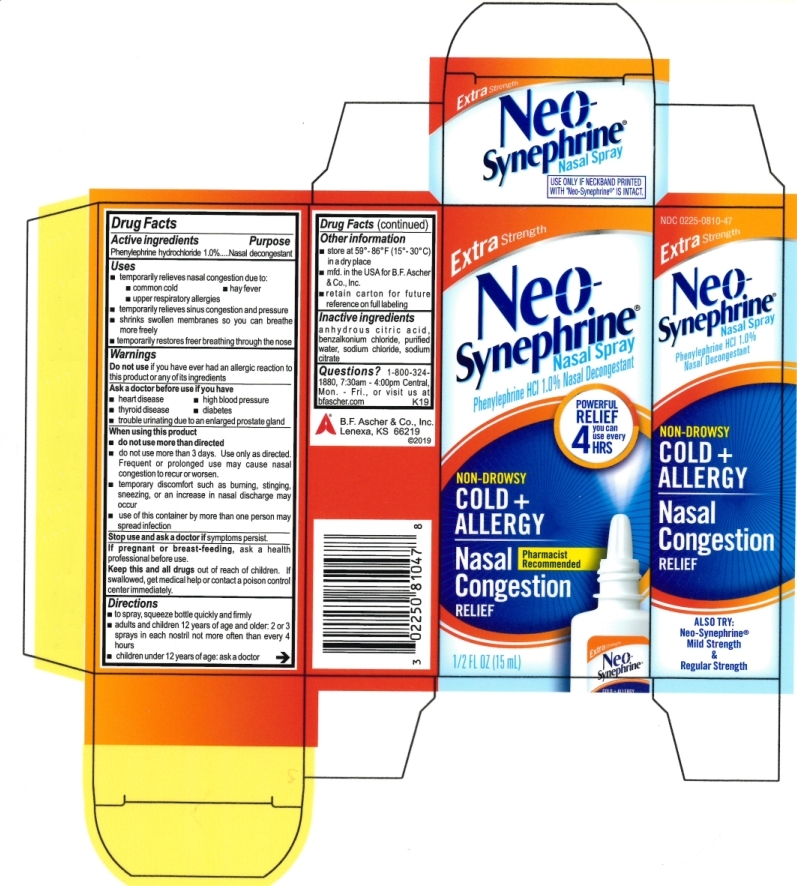 DRUG LABEL: Neo-Synephrine Maximum
NDC: 0225-0810 | Form: SPRAY
Manufacturer: BF ASCHER AND CO INC
Category: otc | Type: HUMAN OTC DRUG LABEL
Date: 20231116

ACTIVE INGREDIENTS: PHENYLEPHRINE HYDROCHLORIDE 1 g/100 mL
INACTIVE INGREDIENTS: BENZALKONIUM CHLORIDE; WATER; SODIUM CITRATE, UNSPECIFIED FORM; SODIUM CHLORIDE; ANHYDROUS CITRIC ACID

Neo-Synephrine Extra

ACTIVE INGREDIENT

Phenylephrine hydrochloride 1.0%

PURPOSE

Nasal decongestant

INDICATIONS AND USAGE

Temporarily relieves nasal congestion due to:

- common cold
- hay fever
- upper respiratory allergies

Temporarily relieves sinus congestion and pressure

Shrinks swollen membranes so you can breathe more freely

Temporarily restores freer breathing through the nose.

When using this product:

- temporary discomfort such as burning, stinging, sneezing, or an increase in nasal discharge may occur.
- use of this container by more than one person may spread infection.
- use only as directed. Frequent or prolonged use may cause nasal congestion to recur or worsen.

Do not use if you have ever had an allergic reaction to this product or any of its ingredients.

Do not use more than directed.

Do not use for more than 3 days.

Ask a doctor before use if you have:

- heart disease
- high blood pressure
- thyroid disease
- diabetes
- trouble urinating due to an enlarged prostate gland

Stop use and as a doctor if symptoms persist.

Stop use and ask a doctor if symptoms persist.

PREGNANCY OR BREAST FEEDING

If pregnant or breast-feeding, ask a health professional before use.

Keep out of reach of children. If swallowed, get medical help or contact a Poison Control Center right away.

DOSAGE AND ADMINISTRATION

- to spray, squeeze bottle quickly and firmly
- adults and children 12 years of age and older: 2 or 3 sprays in each nostril not more often then every 4 hours
- Children under 12 years of age: ask a doctor

STORAGE AND HANDLING

- Store at room temperature, 59º - 86º F (15º -30º C)
- Retain carton for future reference on full labeling

INACTIVE INGREDIENT

anhydrous citric acid, benazalkonium chloride, purified water, sodium chloride, sodium citrate

QUESTIONS

Call 1-800-324-1880, 7:30 - 4:00 Central, Monday - Friday, or visit www.bfascher.com